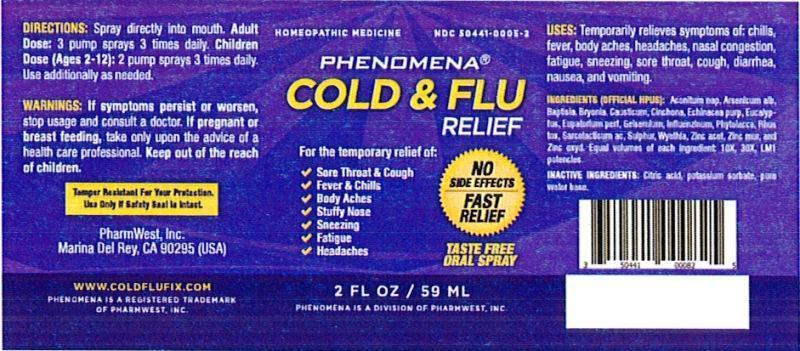 DRUG LABEL: Cold and Flu Relief
NDC: 50441-0005 | Form: LIQUID
Manufacturer: PharmWest Inc.
Category: homeopathic | Type: HUMAN OTC DRUG LABEL
Date: 20140805

ACTIVE INGREDIENTS: ACONITUM NAPELLUS 10 [hp_X]/59 mL; ARSENIC TRIOXIDE 10 [hp_X]/59 mL; BAPTISIA TINCTORIA ROOT 10 [hp_X]/59 mL; BRYONIA ALBA ROOT 10 [hp_X]/59 mL; CAUSTICUM 10 [hp_X]/59 mL; CINCHONA OFFICINALIS BARK 10 [hp_X]/59 mL; ECHINACEA PURPUREA 10 [hp_X]/59 mL; EUCALYPTUS GLOBULUS LEAF 10 [hp_X]/59 mL; EUPATORIUM PERFOLIATUM FLOWERING TOP 10 [hp_X]/59 mL; GELSEMIUM SEMPERVIRENS ROOT 10 [hp_X]/59 mL; INFLUENZA A VIRUS 10 [hp_X]/59 mL; INFLUENZA B VIRUS 10 [hp_X]/59 mL; PHYTOLACCA AMERICANA ROOT 10 [hp_X]/59 mL; TOXICODENDRON PUBESCENS LEAF 10 [hp_X]/59 mL; LACTIC ACID, L- 10 [hp_X]/59 mL; SULFUR 10 [hp_X]/59 mL; WYETHIA HELENIOIDES ROOT 10 [hp_X]/59 mL; ZINC ACETATE ANHYDROUS 10 [hp_X]/59 mL; ZINC CHLORIDE 10 [hp_X]/59 mL; ZINC OXIDE 10 [hp_X]/59 mL
INACTIVE INGREDIENTS: CITRIC ACID MONOHYDRATE; POTASSIUM SORBATE; WATER

Cold and Flu Relief

INDICATIONS AND USAGE

Uses: Temporarily relieves symptoms of: chills, fever, body aches, headaches, nasal congestion, fatigue, sneezing, sore throat, cough, diarrhea, nausea, and vomiting.

ACTIVE INGREDIENT

Ingredients: (Official HPUS): Aconitum napellus, Arsenicum album, Baptisia tinctoria, Bryonia, Causticum, Cinchona officinalis, Echinacea purpurea, Eucalyptus globulus, Eupatorium perfoliatum, Gelsemium sempervirens, Influenzinum, Phytolacca decandra, Rhus toxicodendron, Sarcolacticum acidum, Sulphur, Wyethia helenioides, Zincum aceticum, Zincum muriaticum, Zincum oxydatum. Equal volumes of each ingredient: 10X, 30X, LM1 potencies.

INACTIVE INGREDIENT

Inactive ingredients: Citric acid, potassium sorbate, pure water base.

DOSAGE AND ADMINISTRATION

Directions: Spray directly into mouth.

Adult Dose: 3 pump sprays 3 times daily.

Children's Dose (ages 2-12): 2 pump sprays, 3 times daily.

Use additionally as needed.

WARNINGS

Warnings: If symptoms persist or worsen, stop usage and consult a physician. If pregnant or breast-feeding, take only upon advice of a healthcare professional.

Keep out of the reach of children.

OTHER SAFETY INFORMATION

Tamper resistant for your protection. Use only if safety seal is intact.

PURPOSE

Uses: Temporarily relieves symptoms of:

- Sore Throat & Cough
- Fever & Chills
- Body Aches
- Stuffy Nose
- Sneezing
- Fatigue
- Headaches